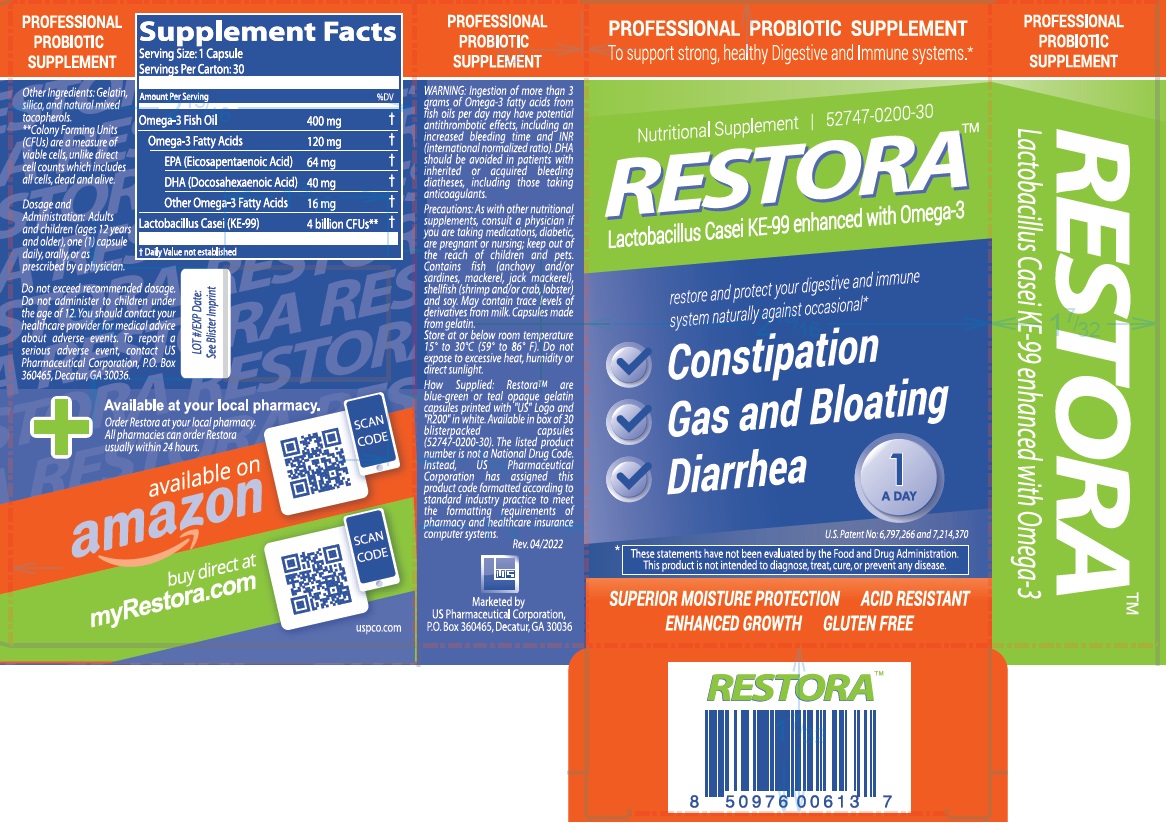 DRUG LABEL: RESTORA
NDC: 52747-200 | Form: CAPSULE
Manufacturer: U.S. PHARMACEUTICAL CORPORATION
Category: other | Type: DIETARY SUPPLEMENT
Date: 20220826

ACTIVE INGREDIENTS: FISH OIL 400 mg/1 1; LACTICASEIBACILLUS CASEI 45 mg/1 1
INACTIVE INGREDIENTS: FD&C GREEN NO. 3; GELATIN, UNSPECIFIED; TOCOPHEROL; SILICON DIOXIDE; TITANIUM DIOXIDE

RESTORA

STATEMENT OF IDENTITY

Supplement Facts; Serving Size: 1 Capsule; Servings Per Carton: 30
Amount Per Serving |  | %DV
Omega-3 Fish Oil | 400 mg | †
Omega-3 Fatty Acids | 120 mg | †
EPA (Eicosapentaenoic Acid) | 64 mg | †
DHA (Docosahexaenoic Acid) | 40 mg | †
Other Omega-3 Fatty Acids | 16 mg | †
Lactobacillus Casei (KE-99) | 4 billion CFUs** | †
† Daily Value not established

Other Ingredients: Gelatin, silica, and natural mixed tocopherols.
**Colony Forming Units (CFUs) are a measure of viable cells, unlike direct cell counts which includes all cells, dead and alive.

WARNINGS

WARNING: Ingestion of more than 3 grams of Omega-3 fatty acids from fish oils per day may have potential antithrombotic effects, including an increased bleeding time and INR (international normalized ratio). DHA should be avoided in patients with inherited or acquired bleeding diatheses, including those taking anticoagulants.

PRECAUTIONS

Precautions: As with other nutritional supplements, consult a physician if you are taking medications, diabetic, are pregnant or nursing; keep out of reach of children and pets. Contains fish (anchovy and/or sardines, mackerel, jack mackerel), shellfish (shrimp and/or crab, lobster) and soy. May contain trace levels of derivatives from milk. Capsules made from gelatin.

SAFE HANDLING WARNING

Store at or below room temperature 15° to 30°C (59° to 86° F). Do not expose to excessive heat, humidity or direct sunlight.

How Supplied: Restora™ are blue-green or teal opaque gelatin capsules printed with "US" Logo and "R200" in white. Available in box of 30 blisterpacked capsules (52747-0200-30). The listed product number is not a National Drug Code. Instead, US Pharmaceutical Corporation has assigned this product code formatted according to standard industry practice to meet the formatting requirements of pharmacy and healthcare insurance computer systems.

Rev.04/2022

Marketed by
US Pharmaceutical Corporation,
P.O.Box 360465, Decatur, GA 30036

Available at your local pharmacy.

Order Restora at your local pharmacy.
All pharmacies can order Restora usually within 24 hours.

available on amazon

buy direct at myRestora.com

uspco.com

Dosage and Administration: Adults and children (ages 12 years and older), one (1) capsule daily, orally, or as prescribed by a physician.

Do not exceed recommended dosage. Do not administer to children under the age of 12. You should contact your healthcare provider for medical advice about adverse events. To report a serious adverse event, contact US Pharmaceutical Corporation, P.O. Box 360465, Decatur, GA 30036.

HEALTH CLAIM

Nutritional Supplement

Lactobacillus Casei KE-99 enhanced with Omega-3

restore and protect your digestive and immune system naturally against occasional*

√ Constipation

√ Gas and Bloating

√ Diarrhea

1 A DAY

U.S. Patent No:6,797,266 and 7,214,370

*

These statements have not been evaluated by the Food and Drug Administration.

This product is not intended to diagnose, treat, cure, or prevent any disease.

SUPERIOR MOISTURE PROTECTION ACID RESISTANT

ENHANCED GROWTH GLUTEN FREE

PROFESSIONAL PROBIOTIC SUPPLEMENT
To support strong, healthy Digestive and Immune systems.*